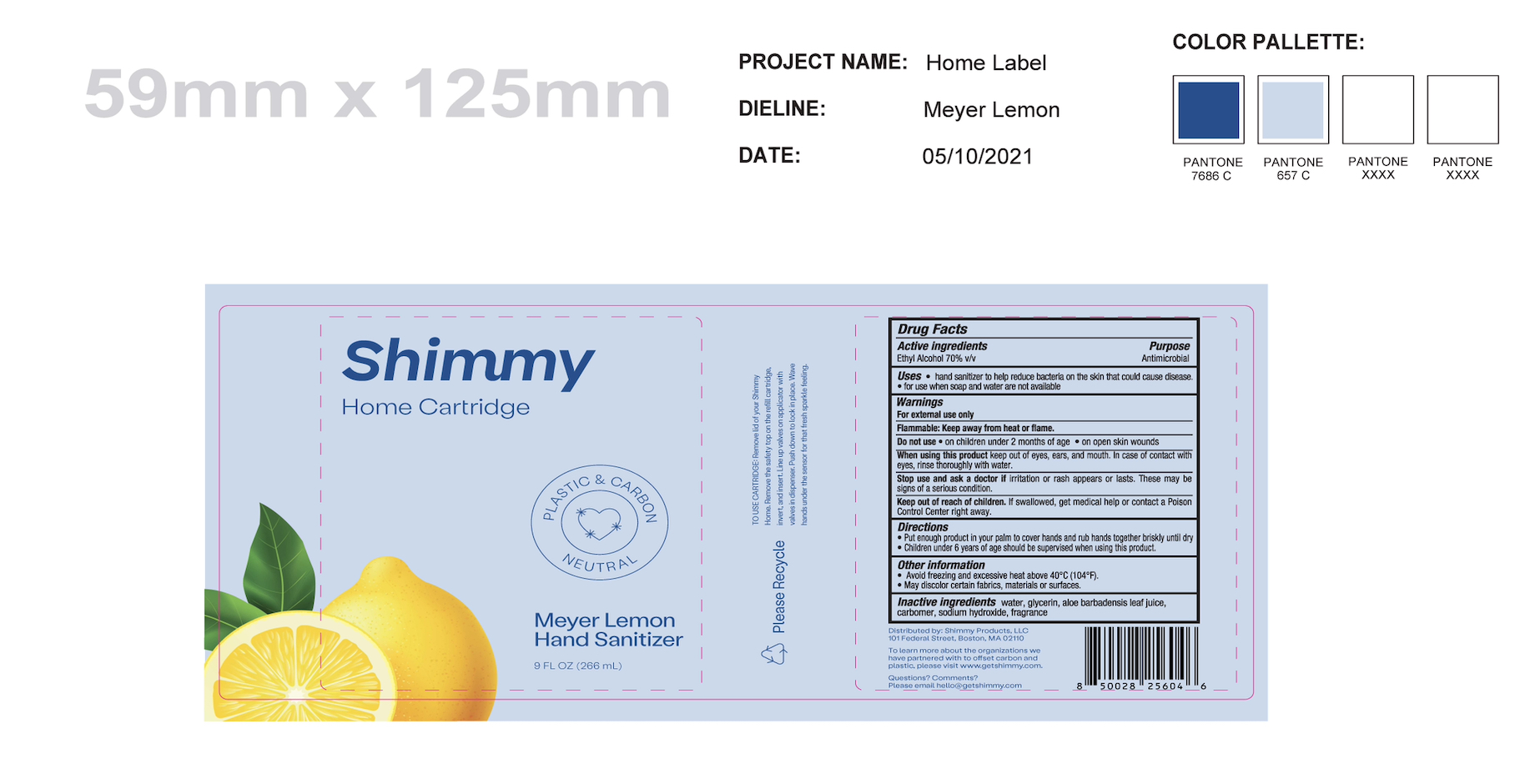 DRUG LABEL: Shimmy Home Cartridge
NDC: 58418-118 | Form: GEL
Manufacturer: Tropical Enterprises International, Inc.
Category: otc | Type: HUMAN OTC DRUG LABEL
Date: 20240102

ACTIVE INGREDIENTS: ALCOHOL 186 mL/266 mL
INACTIVE INGREDIENTS: GLYCERIN; TROLAMINE; FRAGRANCE LEMON ORC2001060; ACRYLATES/C10-30 ALKYL ACRYLATE CROSSPOLYMER (60000 MPA.S); WATER

Get Shimmy Home Cartridge
Meyer Lemon

Active Ingredients. Purpose

Ethyl Alcohol 70%v/v Antimicrobial

Purpose Antimicrobial

INDICATIONS AND USAGE

Uses * hand sanitizer to help reduce bacteria on the skin that could cause disease.

- for use when soap and water are not available

Warnings:

For external use only.

Flammable: Keep away from heat or flame.

Do not use * on children under 2 months of age * on open skin wounds

When using this product keep out of eyes, ears, and mouth. In case of contact with eyes, rinse thoroughly with water.

Stop use and aska doctor if irritation or rash appears or lasts. These may be signs of a serious condition.

Keep out of reach of children. If swallowed, get medical help or contact a Poison

Control Center right away.

Directions

- Put enough product in your palm to cover hands and rub hands together briskly until dry
- Children under 6 years of age should be supervised when using this product.

Other information

- Avoid freezing and excessive heat above 40°C (104°F).
- May discolor certain fabrics, materials or surfaces.

INACTIVE INGREDIENT

Inactive Ingredients water, glycerin, acrylates/C10-30 alkyl acrylate

crosspolymer, triethanolamine, fragrance.